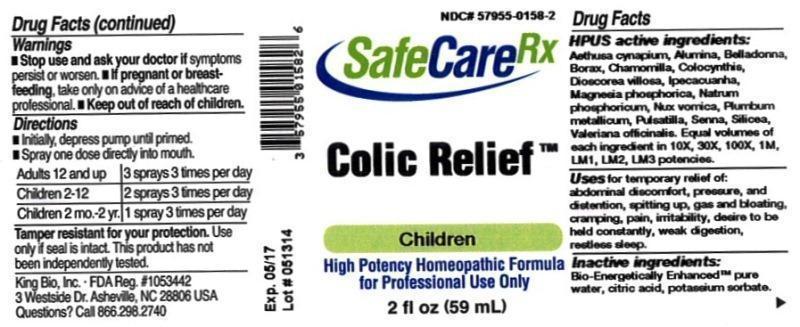 DRUG LABEL: Colic Relief
NDC: 57955-0158 | Form: LIQUID
Manufacturer: King Bio Inc.
Category: homeopathic | Type: HUMAN OTC DRUG LABEL
Date: 20150309

ACTIVE INGREDIENTS: AETHUSA CYNAPIUM 10 [hp_X]/59 mL; ALUMINUM OXIDE 10 [hp_X]/59 mL; ATROPA BELLADONNA 10 [hp_X]/59 mL; SODIUM BORATE 10 [hp_X]/59 mL; MATRICARIA RECUTITA 10 [hp_X]/59 mL; CITRULLUS COLOCYNTHIS FRUIT PULP 10 [hp_X]/59 mL; DIOSCOREA VILLOSA TUBER 10 [hp_X]/59 mL; IPECAC 10 [hp_X]/59 mL; MAGNESIUM PHOSPHATE, DIBASIC TRIHYDRATE 10 [hp_X]/59 mL; SODIUM PHOSPHATE, DIBASIC, HEPTAHYDRATE 10 [hp_X]/59 mL; STRYCHNOS NUX-VOMICA SEED 10 [hp_X]/59 mL; LEAD 10 [hp_X]/59 mL; PULSATILLA VULGARIS 10 [hp_X]/59 mL; SENNA LEAF 10 [hp_X]/59 mL; SILICON DIOXIDE 10 [hp_X]/59 mL; VALERIAN 10 [hp_X]/59 mL
INACTIVE INGREDIENTS: WATER; CITRIC ACID MONOHYDRATE; POTASSIUM SORBATE

Colic Relief

Drug Facts

____________________________________________________________________________________________________________________

HPUS active ingredients: Aethusa cynapium, Alumina, Belladonna, Borax, Chamomilla, Colocynthis, Dioscorea villosa, Ipecacuanha, Magnesia phosphorica, Natrum phosphoricum, Nux vomica, Plumbum metallicum, Pulsatilla, Senna, Silicea, Valeriana officinalis. Equal volumes of each ingredient in 10X, 30X, 100X, 1M, LM1, LM2, LM3 potencies.

INDICATIONS AND USAGE

Uses for temporary relief of: abdominal discomfort, pressure, and distention, spitting up, gas and bloating, cramping, pain, irritability, desire to be held constantly, weak digestion, restless sleep.

INACTIVE INGREDIENT

Inactive ingredients: Bio-Energetically Enhanced pure water, citric acid, potassium sorbate.

Warnings

- Stop use and ask your doctor if symptoms persist or worsen.
- If pregnant or breast-feeding, take only on advice of a healthcare professional.

- Keep out of reach of children.

Directions:

- Initially, depress pump until primed.
- Spray one dose directly into mouth.
- Adults 12 and up: 3 sprays 3 times per day.
- Children 2-12: 2 sprays 3 times per day.
- Children 2 mo-2 yr: 1 spray 3 times per day.

OTHER SAFETY INFORMATION

Tamper resistant for your protection. Use only if safety seal is intact. This product has not been independently tested.

PURPOSE

Uses for temporary relief of:

- abdominal discomfort
- pressure and distention
- spitting up
- gas
- bloating
- cramping
- pain
- irritability
- desire to be held constantly
- weak digestion
- restless sleep